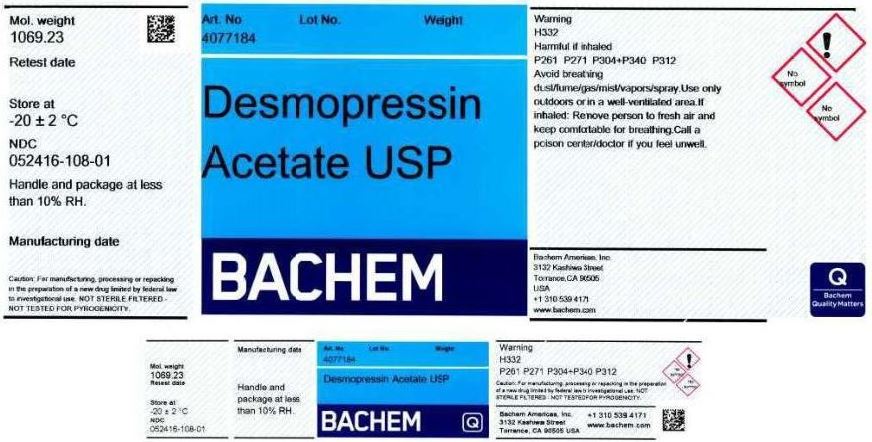 DRUG LABEL: Desmopressin Acetate
NDC: 52416-108 | Form: POWDER
Manufacturer: Bachem Americas, Inc.
Category: other | Type: BULK INGREDIENT
Date: 20241227

ACTIVE INGREDIENTS: DESMOPRESSIN ACETATE 1 g/1 g

Product listing for Desmopressin Acetate, USP